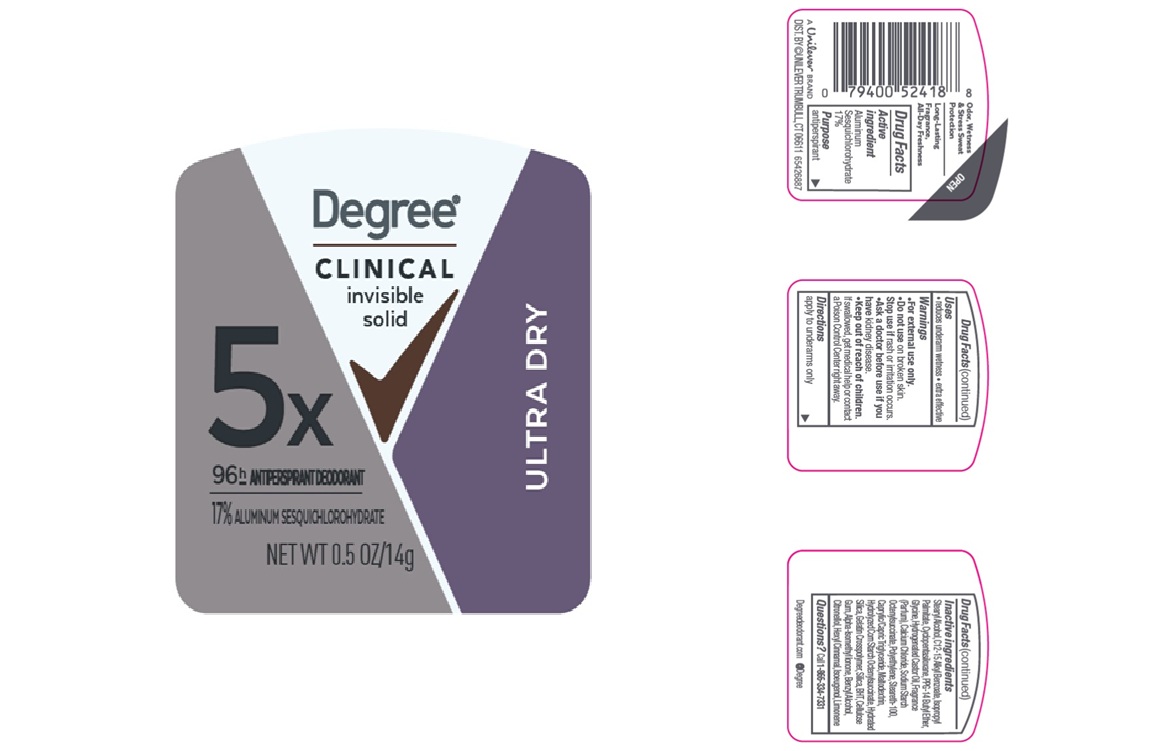 DRUG LABEL: Degree Clinical
NDC: 64942-2424 | Form: STICK
Manufacturer: Conopco Inc. d/b/a/ Unilever
Category: otc | Type: HUMAN OTC DRUG LABEL
Date: 20260218

ACTIVE INGREDIENTS: ALUMINUM SESQUICHLOROHYDRATE 17 g/100 g
INACTIVE INGREDIENTS: STEARYL ALCOHOL; PPG-14 BUTYL ETHER; STEARETH-100; C12-15 ALKYL BENZOATE; ALPHA-ISOMETHYL IONONE; CALCIUM CHLORIDE; MALTODEXTRIN; ISOEUGENOL; SILICA; ISOPROPYL PALMITATE; HYDRATED SILICA; CYCLOPENTASILOXANE; CAPRYLIC/CAPRIC TRIGLYCERIDE; BHT; GLYCINE; BENZYL ALCOHOL; CITRONELLOL; LIMONENE, (+)-; HYDROGENATED CASTOR OIL; CELLULOSE GUM; POLYETHYLENE; HEXYL CINNAMAL

Degree Clinical Ultra Dry Invisible Solid 96H Antiperspirant Deodorant

DESCRIPTION

Degree Clinical Ultra Dry Invisible Solid 96H Antiperspirant Deodorant

ACTIVE INGREDIENT

Aluminum Sesquichlorohydrate 17%

PURPOSE

Antiperspirant

INDICATIONS AND USAGE

reduces underarm wetness
extra effective

WARNINGS

• For external use only.
• Do not use on broken skin. • Stop use if rash or irritation occurs.• Ask a doctor before use if you have kidney disease. • If swallowed,get medical help or contact a Poison Control Center right away.

• KEEP OUT OF REACH OF CHILDREN.

DOSAGE AND ADMINISTRATION

apply to underarms only

INACTIVE INGREDIENT

Stearyl Alcohol, C12-15 Alkyl Benzoate, Isopropyl Palmitate, Cyclopentasiloxane, PPG-14 Butyl Ether, Glycine, Hydrogenated Castor Oil, Fragrance (Parfum), Calcium Chloride, Sodium Starch Octenylsuccinate, Polyethylene, Steareth-100, Caprylic/Capric Triglyceride, Maltodextrin, Hydrolyzed Corn Starch Octenylsuccinate, Hydrated Silica, Gelatin Crosspolymer, Silica, BHT, Cellulose
Gum, Alpha-Isomethyl Ionone, Benzyl Alcohol, Citronellol, Hexyl Cinnamal, Isoeugenol, Limonene

QUESTIONS

Call 1-866-334-7331